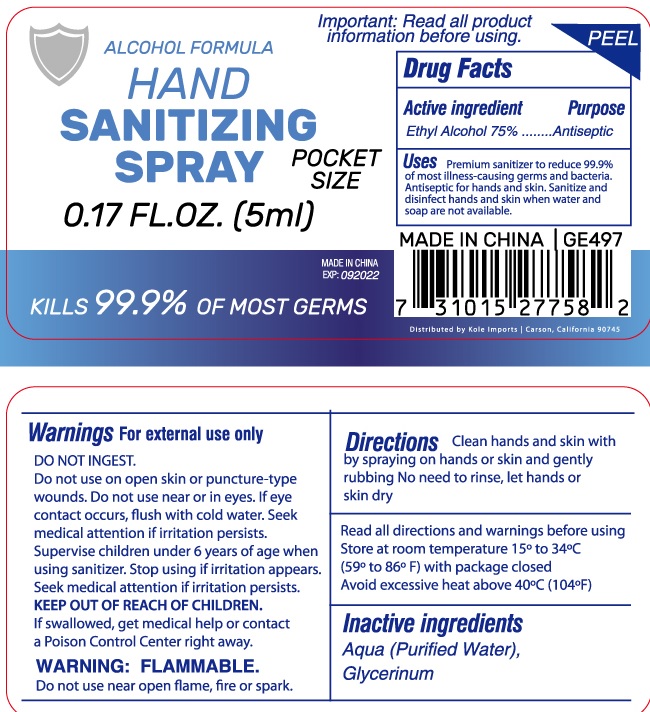 DRUG LABEL: Hand Sanitizing
NDC: 75329-1001 | Form: SPRAY
Manufacturer: Ningbo Lizi Commodity Co., Ltd.
Category: otc | Type: HUMAN OTC DRUG LABEL
Date: 20200826

ACTIVE INGREDIENTS: ALCOHOL 45 mL/60 mL
INACTIVE INGREDIENTS: WATER; GLYCERIN

Hand Sanitizer

Active Ingredient(s)

Ethyl Alcohol .......... 75% v/v.

Purpose

Antiseptic

Use

Premiun sanitizer to reduce 99.9% of most illness-causing germs and bacteria. Antiseptic for hands and skin. Sanitize and disinfect hands and skin when soap and water are not available.

Warnings

For external use only. Flammable. Keep away from heat or flame

Do not use

on open skin or puncture-type wounds.

Stop use and ask a doctor if irritation appears.

Keep out of reach of children. If swallowed, get medical help or contact a Poison Control Center right away.

direction

Clean hands annd skin with by spraying on hands and skin and gently rubbing No need to rinse, let hands or skin dry

Other information

read all directions and warnings before using

Store at room temperature 15℃ to 34℃ （59 ℉ to 86℉）with package closed.

Avoid excessive heat above 40℃ (114℉）

Inactive ingredients

Aqua (Purified Water), Glycerinum